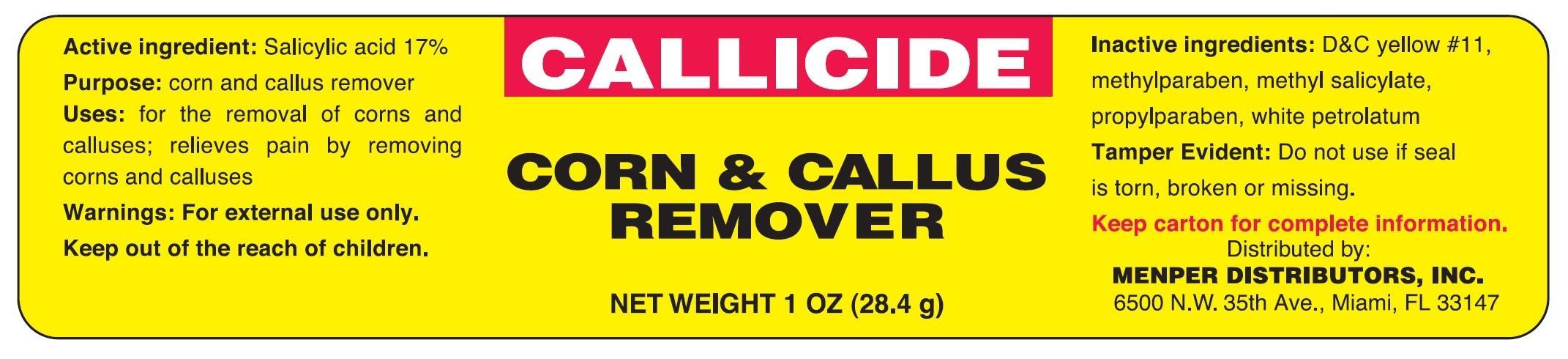 DRUG LABEL: Callicide Corn and Callus Remover
NDC: 53145-022 | Form: OINTMENT
Manufacturer: Menper Distributors, Inc.
Category: otc | Type: HUMAN OTC DRUG LABEL
Date: 20130916

ACTIVE INGREDIENTS: SALICYLIC ACID 5 g/1 g
INACTIVE INGREDIENTS: D&C YELLOW NO. 11; METHYLPARABEN; METHYL SALICYLATE; PROPYLPARABEN; PETROLATUM

Active ingredient

Salicylic acid 17%

Purpose

Corn and callus remover

Uses

for the removal of corns and calluses; relieves pain by removing corns and calluses.

Warnings:

For external use only.

Keep out of reach of children.

Inactive ingredients

D&C yellow #11, methylparaben, methyl salicylate, propylparaben, white petrolatum

DO NOT USE

Tamper Evident

Do not use if seal is broken or missing.

Directions

Apply a thin coat of the medication to cover the entire wart, callus, or corn using the applicator if provided. Be careful to apply it only to the affected area and not the surrounding skin. Let dry for 5 minutes. Repeat this procedure 1 to 2 times daily for up to 2 weeks for corns and calluses and 12 weeks for warts or as directed by your doctor.